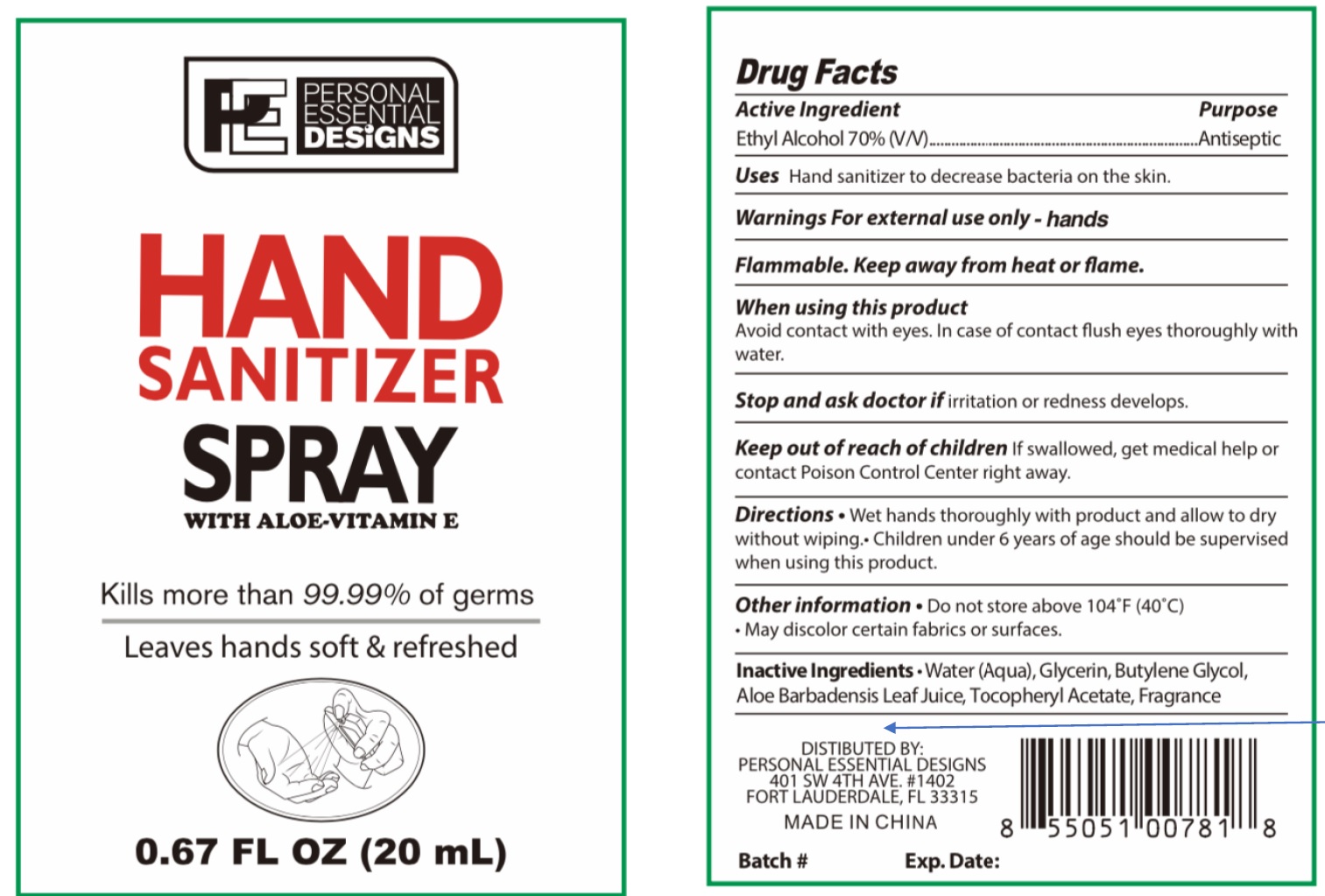 DRUG LABEL: Hand Sanitizer With Aloe and Vitamin E
NDC: 74294-001 | Form: LIQUID
Manufacturer: Personal Essential Designs, LLC
Category: otc | Type: HUMAN OTC DRUG LABEL
Date: 20200702

ACTIVE INGREDIENTS: ALCOHOL 0.7 mL/1 mL
INACTIVE INGREDIENTS: WATER; GLYCERIN; BUTYLENE GLYCOL; ALOE VERA LEAF; .ALPHA.-TOCOPHEROL ACETATE

Hand Sanitizer Spray With Aloe and Vitamin E

Active Ingredient

Ethyl Alcohol 70% (V/V)

Purpose

Antiseptic

Uses

Hand sanitizer to decrease bacteria on the skin.

Warnings

For external use only - hands

Flammable. Keep away from heat or flame.

When using this product

Avoid contact with eyes. In case of contact flush eyes thoroughly with water.

Stop and ask doctor if

irritation or redness develops.

Keep out of reach of children

If swallowed, get medical help or contact Poison Control Center right away.

Directions

- Wet hands thoroughly with product and allow to dry without wiping.
- Children under 6 years of age should be supervised when using this product.

Other information

- Do not store above 104°F (40°C)
- May discolor certain fabrics or surfaces.

Inactive Ingredients

Water (Aqua), Glycerin, Butylene Glycol, Aloe barbadensis Leaf juice, Tocopheryl Acetate, Fragrance